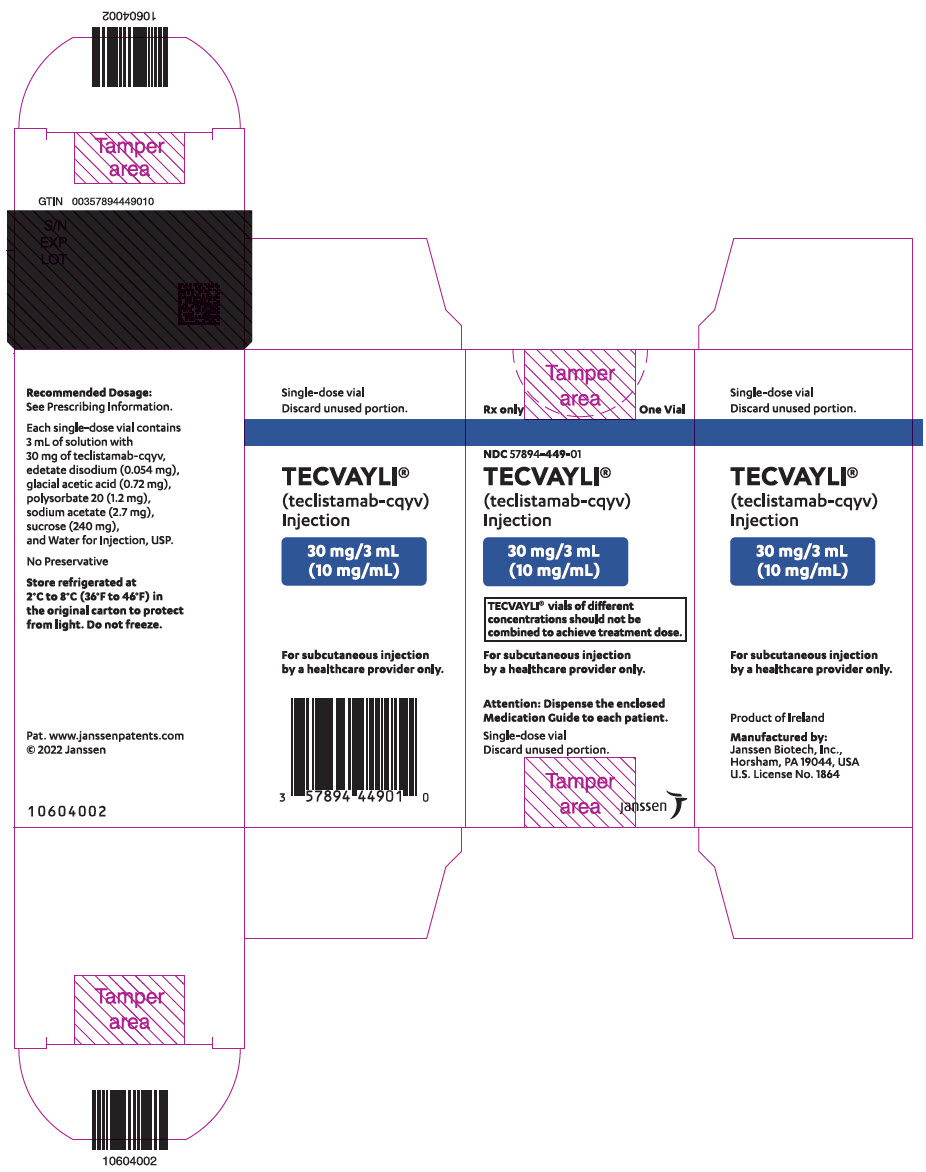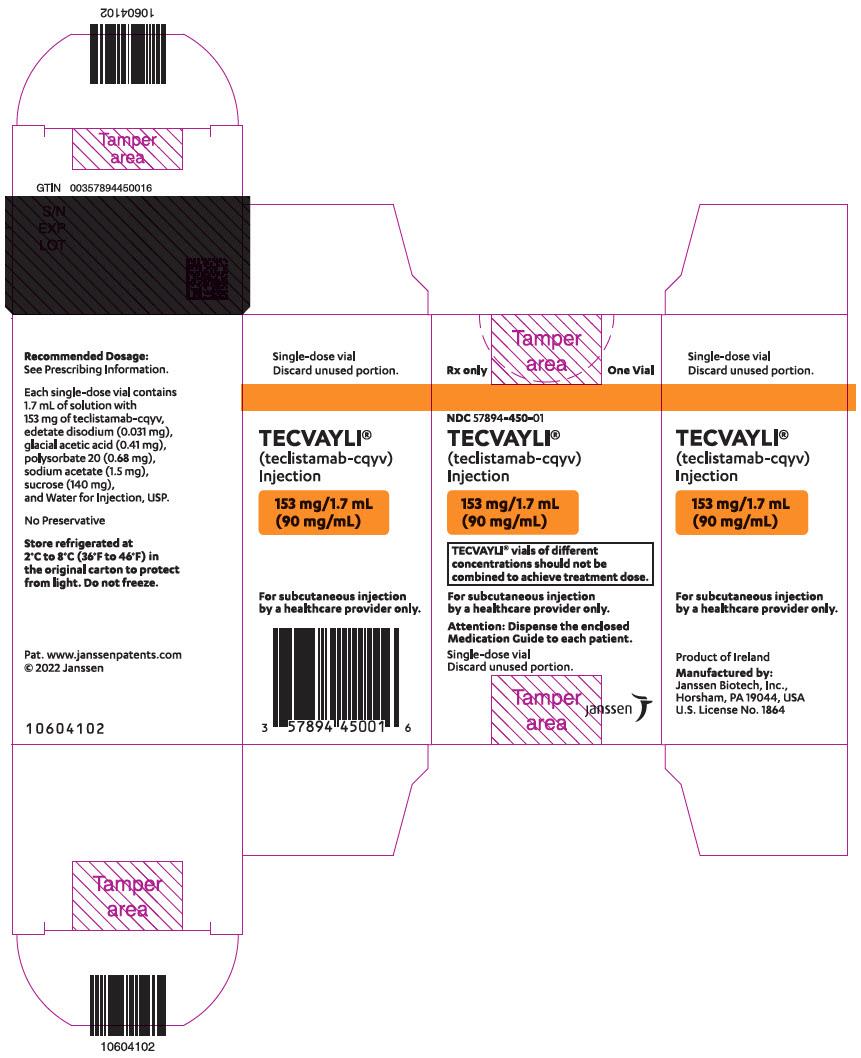 DRUG LABEL: TECVAYLI
NDC: 57894-449 | Form: INJECTION
Manufacturer: Janssen Biotech, Inc.
Category: prescription | Type: HUMAN PRESCRIPTION DRUG LABEL
Date: 20250826

ACTIVE INGREDIENTS: TECLISTAMAB 10 mg/1 mL
INACTIVE INGREDIENTS: SODIUM ACETATE; ACETIC ACID; SUCROSE; POLYSORBATE 20; EDETATE DISODIUM; WATER

HIGHLIGHTS OF PRESCRIBING INFORMATION

These highlights do not include all the information needed to use TECVAYLI safely and effectively. See full prescribing information for TECVAYLI.
TECVAYLI®(teclistamab-cqyv) injection, for subcutaneous use
Initial U.S. Approval: 2022

RECENT MAJOR CHANGES

Boxed Warnings | 8/2025
Dosage and Administration, Recommended Dosage (2.1) | 2/2024
Dosage and Administration, Restarting TECVAYLI after Dosage Delay (2.3) | 11/2024
Dosage and Administration, Preparation and Administration (2.5) | 2/2024
Warnings and Precautions, Neurologic Toxicity including ICANS (5.2) | 8/2025

WARNING: CYTOKINE RELEASE SYNDROME and NEUROLOGIC TOXICITY including IMMUNE EFFECTOR CELL-ASSOCIATED NEUROTOXICITY SYNDROME

See full prescribing information for complete boxed warning.

Cytokine release syndrome (CRS), including life-threatening or fatal reactions, can occur in patients receiving TECVAYLI. Initiate treatment with TECVAYLI step-up dosing schedule to reduce risk of CRS. Withhold TECVAYLI until CRS resolves or permanently discontinue based on severity. (2.1, 2.4, 5.1)

Neurologic toxicity, including Immune Effector Cell-Associated Neurotoxicity Syndrome (ICANS) and serious, life-threatening or fatal reactions, can occur in patients receiving TECVAYLI. Monitor patients for signs or symptoms of neurologic toxicity, including ICANS, during treatment. Withhold TECVAYLI until neurologic toxicity resolves or permanently discontinue based on severity. (2.4, 5.2)

TECVAYLI is available only through a restricted program called the TECVAYLI and TALVEY Risk Evaluation and Mitigation Strategy (REMS). (5.3)

1 INDICATIONS AND USAGE

TECVAYLI is a bispecific B-cell maturation antigen (BCMA)-directed CD3 T-cell engager indicated for the treatment of adult patients with relapsed or refractory multiple myeloma who have received at least four prior lines of therapy, including a proteasome inhibitor, an immunomodulatory agent and an anti-CD38 monoclonal antibody.

This indication is approved under accelerated approval based on response rate. Continued approval for this indication may be contingent upon verification and description of clinical benefit in a confirmatory trial(s). (1)

2 DOSAGE AND ADMINISTRATION

TECVAYLI Recommended Dosing Schedule (2.1)
Dosing Schedule | Day | Dose
All Patients
Step-up Dosing Schedule | Day 1 | Step-up dose 1 | 0.06 mg/kg
Step-up Dosing Schedule | Day 4 [Step-up dose 2 may be given between 2 to 4 days after step-up dose 1 and may be given up to 7 days after step-up dose 1 to allow for resolution of adverse reactions.] | Step-up dose 2 | 0.3 mg/kg
Step-up Dosing Schedule | Day 7 [First treatment dose may be given between 2 to 4 days after step-up dose 2 and may be given up to 7 days after step-up dose 2 to allow for resolution of adverse reactions.] | First treatment dose | 1.5 mg/kg
Weekly Dosing Schedule | One week after first treatment dose and weekly thereafter | Subsequent treatment doses | 1.5 mg/kg once weekly
Patients who have achieved and maintained a complete response or better for a minimum of 6 months
Biweekly (every two weeks) dosing schedule | The dosing frequency may be decreased to 1.5 mg/kg every two weeks

- For subcutaneous injection only. (2.1)
- Patients should be hospitalized for 48 hours after administration of all doses within the TECVAYLI step-up dosing schedule. (2.1)
- Administer pretreatment medications as recommended. (2.2)
- Refer to Tables 7, 8, and 9 to determine the dosage based on predetermined weight ranges. (2.5)
- See Full Prescribing Information for instructions on preparation and administration. (2.5)

3 DOSAGE FORMS AND STRENGTHS

Injection

- 30 mg/3 mL (10 mg/mL) in a single-dose vial (3)
- 153 mg/1.7 mL (90 mg/mL) in a single-dose vial (3)

4 CONTRAINDICATIONS

None. (4)

5 WARNINGS AND PRECAUTIONS

- Hepatotoxicity: Can cause hepatotoxicity, including fatalities. Monitor liver enzymes and bilirubin at baseline and during treatment as clinically indicated. (5.4)
- Infections: Can cause severe, life-threatening, or fatal infections. Monitor patients for signs and symptoms of infection and treat appropriately. Withhold in patients with active infection during the step-up dosing schedule. (2.4, 5.5)
- Neutropenia: Monitor complete blood cell counts at baseline and periodically during treatment. (5.6)
- Hypersensitivity and Other Administration Reactions: Systemic administration-related reactions and local injection site reactions can occur. Withhold or consider permanent discontinuation based on severity. (2.4, 5.7)
- Embryo-Fetal Toxicity: May cause fetal harm. Advise females of reproductive potential of the potential risk to the fetus and to use effective contraception. (5.8, 8.1, 8.3)

6 ADVERSE REACTIONS

The most common adverse reactions (≥20%) are pyrexia, cytokine release syndrome, musculoskeletal pain, injection site reaction, fatigue, upper respiratory tract infection, nausea, headache, pneumonia, and diarrhea.

The most common Grade 3 to 4 laboratory abnormalities (≥20%) are decreased lymphocytes, decreased neutrophils, decreased white blood cells, decreased hemoglobin, and decreased platelets. (6.1)

To report SUSPECTED ADVERSE REACTIONS, contact Janssen Biotech, Inc. at 1-800-526-7736 or FDA at 1-800-FDA-1088 or www.fda.gov/medwatch.

8 USE IN SPECIFIC POPULATIONS

Lactation: Advise not to breastfeed. (8.2)

FULL PRESCRIBING INFORMATION

WARNING: CYTOKINE RELEASE SYNDROME and NEUROLOGIC TOXICITY including IMMUNE EFFECTOR CELL-ASSOCIATED NEUROTOXICITY SYNDROME

Cytokine release syndrome (CRS), including life-threatening or fatal reactions, can occur in patients receiving TECVAYLI. Initiate treatment with TECVAYLI step-up dosing schedule to reduce risk of CRS. Withhold TECVAYLI until CRS resolves or permanently discontinue based on severity [see Dosage and Administration (2.1, 2.4)and Warnings and Precautions (5.1)] .

Neurologic toxicity, including Immune Effector Cell-Associated Neurotoxicity Syndrome (ICANS) and serious, life-threatening or fatal reactions, can occur with TECVAYLI. Monitor patients for signs or symptoms of neurologic toxicity, including ICANS, during treatment. Withhold TECVAYLI until neurologic toxicity resolves or permanently discontinue based on severity [see Dosage and Administration (2.4)and Warnings and Precautions (5.2)] .

Because of the risk of CRS and neurologic toxicity, including ICANS, TECVAYLI is available only through a restricted program under a Risk Evaluation and Mitigation Strategy (REMS) called the TECVAYLI and TALVEY REMS [see Warnings and Precautions (5.3)] .

1 INDICATIONS AND USAGE

TECVAYLI is indicated for the treatment of adult patients with relapsed or refractory multiple myeloma who have received at least four prior lines of therapy, including a proteasome inhibitor, an immunomodulatory agent and an anti-CD38 monoclonal antibody.

This indication is approved under accelerated approval based on response rate [see Clinical Studies (14)] . Continued approval for this indication may be contingent upon verification and description of clinical benefit in confirmatory trial(s).

2 DOSAGE AND ADMINISTRATION

2.1 Recommended Dosage

For subcutaneous injection only.

The recommended dosing schedule for TECVAYLI is provided in Table 1. The recommended dosage of TECVAYLI is step-up doses of 0.06 mg/kg and 0.3 mg/kg followed by 1.5 mg/kg once weekly until disease progression or unacceptable toxicity. In patients who have achieved and maintained a complete response or better for a minimum of 6 months, the dosing frequency may be decreased to 1.5 mg/kg every two weeks until disease progression or unacceptable toxicity.

Administer pretreatment medications prior to each dose of the TECVAYLI step-up dosing schedule, which includes step-up dose 1, step-up dose 2, and the first treatment dose as described in Table 1 [see Dosage and Administration (2.2)] .

Administer TECVAYLI subcutaneously according to the step-up dosing schedule in Table 1 to reduce the incidence and severity of cytokine release syndrome (CRS). Due to the risk of CRS and neurologic toxicity, including ICANS, patients should be hospitalized for 48 hours after administration of all doses within the TECVAYLI step-up dosing schedule [see Dosage and Administration (2.4)and Warnings and Precautions (5.1, 5.2)] .

Table 1: TECVAYLI Dosing Schedule
Dosing schedule | Day | Dose
All Patients
Step-up dosing schedule [See Table 2 for recommendations on restarting TECVAYLI after dose delays [see Dosage and Administration (2.3)].] | Day 1 | Step-up dose 1 | 0.06 mg/kg
Step-up dosing schedule [See Table 2 for recommendations on restarting TECVAYLI after dose delays [see Dosage and Administration (2.3)].] | Day 4 [Step-up dose 2 may be given between 2 to 4 days after step-up dose 1 and may be given up to 7 days after step-up dose 1 to allow for resolution of adverse reactions.] | Step-up dose 2 | 0.3 mg/kg
Step-up dosing schedule [See Table 2 for recommendations on restarting TECVAYLI after dose delays [see Dosage and Administration (2.3)].] | Day 7 [First treatment dose may be given between 2 to 4 days after step-up dose 2 and may be given up to 7 days after step-up dose 2 to allow for resolution of adverse reactions.] | First treatment dose | 1.5 mg/kg
Weekly dosing schedule | One week after first treatment dose and weekly thereafter | Subsequent treatment doses | 1.5 mg/kg once weekly
Patients who have achieved and maintained a complete response or better for a minimum of 6 months
Biweekly (every two weeks) dosing schedule | The dosing frequency may be decreased to 1.5 mg/kg every two weeks.

Refer to Tables 7, 8, and 9 to determine the dosage based on predetermined weight ranges [see Dosage and Administration (2.5)] .

2.2 Recommended Pretreatment Medications

Administer the following pretreatment medications 1 to 3 hours before each dose of the TECVAYLI step-up dosing schedule, which includes step-up dose 1, step-up dose 2, and the first treatment dose (see Table 1), to reduce the risk of CRS [see Warnings and Precautions (5.1)and Adverse Reactions (6.1)] .

- Corticosteroid (oral or intravenous dexamethasone 16 mg)
- Histamine-1 (H1) receptor antagonist (oral or intravenous diphenhydramine 50 mg or equivalent)
- Antipyretics (oral or intravenous acetaminophen 650 mg to 1,000 mg or equivalent)

Administration of pretreatment medications may be required prior to administration of subsequent doses of TECVAYLI in the following patients:

- Patients who repeat doses within the TECVAYLI step-up dosing schedule following a dose delay [see Dosage and Administration (2.3)].
- Patients who experienced CRS following the prior dose of TECVAYLI [see Dosage and Administration (2.4)].

Prophylaxis for Herpes Zoster Reactivation

Prior to starting treatment with TECVAYLI, consider initiation of antiviral prophylaxis to prevent herpes zoster reactivation per guidelines.

2.3 Restarting TECVAYLI after Dosage Delay

If a dose of TECVAYLI is delayed, restart therapy based on the recommendations in Table 2 and resume the treatment schedule accordingly [see Dosage and Administration (2.1)] . Administer pretreatment medications as indicated in Table 2 .Due to the risk of CRS and neurologic toxicity, including ICANS, patients should be hospitalized for 48 hours after administration of all doses within the TECVAYLI step-up dosing schedule [see Dosage and Administration (2.4)and Warnings and Precautions (5.1, 5.2)].

Table 2: Recommendations for Restarting Therapy with TECVAYLI After Dose Delay
Last dose administered | Time since the last dose administered | Action
Step-up dose 1 | More than 7 days | Restart TECVAYLI step-up dosing schedule at step-up dose 1 (0.06 mg/kg). [Administer pretreatment medications prior to TECVAYLI dose and monitor patients accordingly [see Dosage and Administration (2.2, 2.5)].]
Step-up dose 2 | 8 days to 28 days | Repeat step-up dose 2 (0.3 mg/kg) and continue TECVAYLI step-up dosing schedule.
Step-up dose 2 | More than 28 days [Consider benefit-risk of restarting TECVAYLI in patients who require a dose delay of more than 28 days due to an adverse reaction.] | Restart TECVAYLI step-up dosing schedule at step-up dose 1 (0.06 mg/kg).
Any weekly treatment dose | 28 days or less | Continue TECVAYLI at last treatment dose in weekly schedule (1.5 mg/kg once weekly; see Table 1).
Any weekly treatment dose | 29 days to 56 days | Restart TECVAYLI step-up dosing schedule at step-up dose 2 (0.3 mg/kg).
Any weekly treatment dose | More than 56 days | Restart TECVAYLI step-up dosing schedule at step-up dose 1 (0.06 mg/kg).
Any biweekly (every two weeks) treatment dose | 63 days or less | Continue TECVAYLI at last treatment dose in biweekly schedule (1.5 mg/kg every two weeks; see Table 1).
Any biweekly (every two weeks) treatment dose | 64 days to 112 days | Restart TECVAYLI step-up dosing schedule at step up dose 2 (0.3 mg/kg).
Any biweekly (every two weeks) treatment dose | More than 112 days | Restart TECVAYLI step-up dosing schedule at step-up dose 1 (0.06 mg/kg).

2.4 Dosage Modifications for Adverse Reactions

Dosage reductions of TECVAYLI are not recommended.

Dosage delays may be required to manage toxicities related to TECVAYLI [see Warnings and Precautions (5)].

See Tables 3, 4, and 5for recommended actions for adverse reactions of CRS, neurologic toxicity, and ICANS. See Table 6for recommended actions for other adverse reactions following administration of TECVAYLI.

Management of CRS, Neurologic Toxicity and ICANS

Cytokine Release Syndrome (CRS)

Management recommendations for CRS are summarized in Table 3.

Identify CRS based on clinical presentation [see Warnings and Precautions (5.1)]. Evaluate and treat other causes of fever, hypoxia, and hypotension.

If CRS is suspected, withhold TECVAYLI until CRS resolves. Manage according to the recommendations in Table 3 and consider further management per current practice guidelines. Administer supportive therapy for CRS, which may include intensive care for severe or life-threatening CRS. Consider laboratory testing to monitor for disseminated intravascular coagulation (DIC), hematology parameters, as well as pulmonary, cardiac, renal, and hepatic function.

Table 3: Recommendations for Management of Cytokine Release Syndrome
Grade [Based on American Society for Transplantation and Cellular Therapy (ASTCT) 2019 grading for CRS.] | Presenting Symptoms | Actions
Grade 1 | Temperature ≥100.4 °F (38 °C) [Attributed to CRS. Fever may not always be present concurrently with hypotension or hypoxia as it may be masked by interventions such as antipyretics or anticytokine therapy.] | - Withhold TECVAYLI until CRS resolves. - Administer pretreatment medications prior to next dose of TECVAYLI. [See Table 2 for recommendations on restarting TECVAYLI after dose delays [see Dosage and Administration (2.3)].]
Grade 2 | Temperature ≥100.4 °F (38 °C) with: Hypotension responsive to fluids and not requiring vasopressors, and/or, Oxygen requirement of low-flow nasal cannula [Low-flow nasal cannula is ≤6 L/min, and high-flow nasal cannula is >6 L/min.] or blow-by. | - Withhold TECVAYLI until CRS resolves. - Administer pretreatment medications prior to next dose of TECVAYLI. - Patients should be hospitalized for 48 hours following the next dose of TECVAYLI [see Dosage and Administration (2.1)].
Grade 3 | Temperature ≥100.4 °F (38 °C) with: Hypotension requiring one vasopressor with or without vasopressin, and/or, Oxygen requirement of high-flow nasal cannula , facemask, non-rebreather mask, or Venturi mask. | First Occurrence of Grade 3 CRS with Duration Less than 48 Hours:; - Withhold TECVAYLI until CRS resolves. - Provide supportive therapy, which may include intensive care. - Administer pretreatment medications prior to next dose of TECVAYLI. - Patients should be hospitalized for 48 hours following the next dose of TECVAYLI [see Dosage and Administration (2.1)].
Grade 3 | Temperature ≥100.4 °F (38 °C) with: Hypotension requiring one vasopressor with or without vasopressin, and/or, Oxygen requirement of high-flow nasal cannula , facemask, non-rebreather mask, or Venturi mask. | Recurrent Grade 3 CRS or Grade 3 CRS with Duration 48 Hours or Longer:; - Permanently discontinue TECVAYLI. - Provide supportive therapy, which may include intensive care.
Grade 4 | Temperature ≥100.4 °F (38 °C) with: Hypotension requiring multiple vasopressors (excluding vasopressin), and/or, Oxygen requirement of positive pressure (e.g., continuous positive airway pressure (CPAP), bilevel positive airway pressure (BiPAP), intubation, and mechanical ventilation). | - Permanently discontinue TECVAYLI. - Provide supportive therapy, which may include intensive care.

Neurologic Toxicity and ICANS

Management recommendations for neurologic toxicity and ICANS are summarized in Tables 4 and 5.

At the first sign of neurologic toxicity, including ICANS, withhold TECVAYLI and consider neurology evaluation. Rule out other causes of neurologic symptoms. Provide supportive therapy, which may include intensive care, for severe or life-threatening neurologic toxicities, including ICANS [see Warnings and Precautions (5.2)] . Manage ICANS according to the recommendations in Table 5 and consider further management per current practice guidelines.

Table 4: Recommendations for Management of Neurologic Toxicity (excluding ICANS)
Adverse Reaction | Severity [Based on National Cancer Institute Common Terminology Criteria for Adverse Events (NCI CTCAE), version 4.03.] | Actions
Neurologic Toxicity (excluding ICANS) | Grade 1 | - Withhold TECVAYLI until neurologic toxicity symptoms resolve or stabilize. [See Table 2 for recommendations on restarting TECVAYLI after dose delays [see Dosage and Administration (2.3)].]
Neurologic Toxicity (excluding ICANS) | Grade 2 Grade 3 (First occurrence) | - Withhold TECVAYLI until neurologic toxicity symptoms improve to Grade 1 or less. - Provide supportive therapy.
Neurologic Toxicity (excluding ICANS) | Grade 3 (Recurrent) Grade 4 | - Permanently discontinue TECVAYLI. - Provide supportive therapy, which may include intensive care.

Table 5: Recommendations for Management of Immune Effector Cell-Associated Neurotoxicity Syndrome
Grade [Based on American Society for Transplantation and Cellular Therapy (ASTCT) 2019 grading for ICANS.] | Presenting Symptoms [Management is determined by the most severe event, not attributable to any other cause.] | Actions
Grade 1 | ICE score 7–9 [If patient is arousable and able to perform Immune Effector Cell-Associated Encephalopathy (ICE) Assessment, assess: Orientation (oriented to year, month, city, hospital = 4 points); Naming (name 3 objects, e.g., point to clock, pen, button = 3 points); Following Commands (e.g., "show me 2 fingers" or "close your eyes and stick out your tongue" = 1 point); Writing (ability to write a standard sentence = 1 point; and Attention (count backwards from 100 by ten = 1 point). If patient is unarousable and unable to perform ICE Assessment (Grade 4 ICANS) = 0 points.] , or depressed level of consciousness [Not attributable to any other cause.] : awakens spontaneously. | - Withhold TECVAYLI until ICANS resolves. [See Table 2 for recommendations on restarting TECVAYLI after dose delays [see Dosage and Administration (2.3)].] - Monitor neurologic symptoms and consider consultation with neurologist and other specialists for further evaluation and management, including consideration for starting non-sedating, anti-seizure medicines for seizure prophylaxis.
Grade 2 | ICE score 3–6 , or depressed level of consciousness : awakens to voice. | - Withhold TECVAYLI until ICANS resolves. - Administer dexamethasone [All references to dexamethasone administration are dexamethasone or equivalent.] 10 mg intravenously every 6 hours. Continue dexamethasone use until resolution to Grade 1 or less then taper. - Monitor neurologic symptoms and consider consultation with neurologist and other specialists for further evaluation and management, including consideration for starting non-sedating, anti-seizure medicines for seizure prophylaxis. - Patients should be hospitalized for 48 hours following the next dose of TECVAYLI [see Dosage and Administration (2.1)] .
Grade 3 | ICE score 0–2 , or depressed level of consciousness : awakens only to tactile stimulus, or seizures , either:; - any clinical seizure, focal or generalized, that resolves rapidly, or - non-convulsive seizures on electroencephalogram (EEG) that resolve with intervention,; or raised intracranial pressure: focal/local edema on neuroimaging . | First Occurrence of Grade 3 ICANS:; - Withhold TECVAYLI until ICANS resolves. - Administer dexamethasone 10 mg intravenously every 6 hours. Continue dexamethasone use until resolution to Grade 1 or less, then taper. - Monitor neurologic symptoms and consider consultation with neurologist and other specialists for further evaluation and management, including consideration for starting non-sedating, anti-seizure medicines for seizure prophylaxis. - Provide supportive therapy, which may include intensive care. - Patients should be hospitalized for 48 hours following the next dose of TECVAYLI [see Dosage and Administration (2.1)] .
Grade 3 | ICE score 0–2 , or depressed level of consciousness : awakens only to tactile stimulus, or seizures , either:; - any clinical seizure, focal or generalized, that resolves rapidly, or - non-convulsive seizures on electroencephalogram (EEG) that resolve with intervention,; or raised intracranial pressure: focal/local edema on neuroimaging . | Recurrent Grade 3 ICANS:; - Permanently discontinue TECVAYLI - Administer dexamethasone 10 mg intravenously and repeat dose every 6 hours. Continue dexamethasone use until resolution to Grade 1 or less, then taper. - Monitor neurologic symptoms and consider consultation with neurologist and other specialists for further evaluation and management, including consideration for starting non-sedating, anti-seizure medicines for seizure prophylaxis. - Provide supportive therapy, which may include intensive care.
Grade 4 | ICE score 0 , or depressed level of consciousness : either:; - patient is unarousable or requires vigorous or repetitive tactile stimuli to arouse, or - stupor or coma,; or seizures , either:; - life-threatening prolonged seizure (>5 minutes), or - repetitive clinical or electrical seizures without return to baseline in between,; or motor findings :; - deep focal motor weakness such as hemiparesis or paraparesis,; or raised intracranial pressure/cerebral edema , with signs/symptoms such as:; - diffuse cerebral edema on neuroimaging, or - decerebrate or decorticate posturing, or - cranial nerve VI palsy, or - papilledema, or - Cushing's triad. | - Permanently discontinue TECVAYLI. - Administer dexamethasone 10 mg intravenously and repeat dose every 6 hours. Continue dexamethasone use until resolution to Grade 1 or less, then taper. - Alternatively, consider administration of methylprednisolone 1,000 mg per day intravenously and continue methylprednisolone 1,000 mg per day intravenously for 2 or more days. - Monitor neurologic symptoms and consider consultation with neurologist and other specialists for further evaluation and management, including consideration for starting non-sedating, anti-seizure medicines for seizure prophylaxis. - Provide supportive therapy, which may include intensive care.

Table 6: Recommended Dosage Modifications for Other Adverse Reactions
Adverse Reactions | Severity | Actions
Infections [Based on National Cancer Institute Common Terminology Criteria for Adverse Events (NCI CTCAE), version 4.03.] [see Warnings and Precautions (5.5)] | All Grades | - Withhold TECVAYLI in patients with active infection during the step-up dosing schedule. [See Table 2 for recommendations on restarting TECVAYLI after dose delays [see Dosage and Administration (2.3)].]
Infections [Based on National Cancer Institute Common Terminology Criteria for Adverse Events (NCI CTCAE), version 4.03.] [see Warnings and Precautions (5.5)] | Grade 3 | - Withhold subsequent treatment doses of TECVAYLI (i.e., doses administered after TECVAYLI step-up dosing schedule) until infection improves to Grade 1 or less.
Infections [Based on National Cancer Institute Common Terminology Criteria for Adverse Events (NCI CTCAE), version 4.03.] [see Warnings and Precautions (5.5)] | Grade 4 | - Consider permanent discontinuation of TECVAYLI. - If TECVAYLI is not permanently discontinued, withhold subsequent treatment doses of TECVAYLI (i.e., doses administered after TECVAYLI step-up dosing schedule) until infection improves to Grade 1 or less.
Hematologic Toxicities [see Warnings and Precautions (5.6)and Adverse Reactions (6.1)] | Absolute neutrophil count less than 0.5 × 10^9/L | - Withhold TECVAYLI until absolute neutrophil count is 0.5 × 10^9/L or higher.
Hematologic Toxicities [see Warnings and Precautions (5.6)and Adverse Reactions (6.1)] | Febrile neutropenia | - Withhold TECVAYLI until absolute neutrophil count is 1 × 10^9/L or higher and fever resolves.
Hematologic Toxicities [see Warnings and Precautions (5.6)and Adverse Reactions (6.1)] | Hemoglobin less than 8 g/dL | - Withhold TECVAYLI until hemoglobin is 8 g/dL or higher.
Hematologic Toxicities [see Warnings and Precautions (5.6)and Adverse Reactions (6.1)] | Platelet count less than 25,000/mcL Platelet count between 25,000/mcL and 50,000/mcL with bleeding | - Withhold TECVAYLI until platelet count is 25,000/mcL or higher and no evidence of bleeding.
Other Non-Hematologic Adverse Reactions [see Warnings and Precautions (5.4)and Adverse Reactions (6.1)] | Grade 3 | - Withhold TECVAYLI until adverse reaction improves to Grade 1 or less.
Other Non-Hematologic Adverse Reactions [see Warnings and Precautions (5.4)and Adverse Reactions (6.1)] | Grade 4 | - Consider permanent discontinuation of TECVAYLI. - If TECVAYLI is not permanently discontinued, withhold subsequent treatment doses of TECVAYLI (i.e., doses administered after TECVAYLI step-up dosing schedule) until adverse reaction improves to Grade 1 or less.

2.5 Preparation and Administration

TECVAYLI is intended for subcutaneous use by a healthcare provider only.

TECVAYLI should be administered by a healthcare provider with adequate medical personnel and appropriate medical equipment to manage severe reactions, including CRS and ICANS [see Warnings and Precautions (5.1, 5.2)] .

TECVAYLI is a clear to slightly opalescent, colorless to light yellow solution. Parenteral drug products should be inspected visually for particulate matter and discoloration prior to administration, whenever solution and container permit. Do not use if the solution is discolored, or cloudy, or if foreign particles are present.

TECVAYLI 30 mg/3 mL (10 mg/mL) vial and TECVAYLI 153 mg/1.7 mL (90 mg/mL) vial are supplied as ready-to-use solution that do not need dilution prior to administration.

Do not combine TECVAYLI vials of different concentrations to achieve treatment dose.

Use aseptic technique to prepare and administer TECVAYLI.

Preparation of TECVAYLI

Refer to the following reference tables for the preparation of TECVAYLI.

Refer to Tables 7, 8, and 9 below to determine the dosage based on predetermined weight ranges.

Use Table 7 to determine total dose, injection volume and number of vials required based on patient's actual body weight for step-up dose 1 using TECVAYLI 30 mg/3 mL (10 mg/mL) vial.

Table 7: Step-up Dose 1 (0.06 mg/kg) Injection Volumes using TECVAYLI 30 mg/3 mL (10 mg/mL) Vial
Patient Body Weight (kg) | Total Dose (mg) | Volume of Injection (mL) | Number of Vials (1 vial=3 mL)
35 to 39 | 2.2 | 0.22 | 1
40 to 44 | 2.5 | 0.25 | 1
45 to 49 | 2.8 | 0.28 | 1
50 to 59 | 3.3 | 0.33 | 1
60 to 69 | 3.9 | 0.39 | 1
70 to 79 | 4.5 | 0.45 | 1
80 to 89 | 5.1 | 0.51 | 1
90 to 99 | 5.7 | 0.57 | 1
100 to 109 | 6.3 | 0.63 | 1
110 to 119 | 6.9 | 0.69 | 1
120 to 129 | 7.5 | 0.75 | 1
130 to 139 | 8.1 | 0.81 | 1
140 to 149 | 8.7 | 0.87 | 1
150 to 160 | 9.3 | 0.93 | 1

Use Table 8 to determine total dose, injection volume and number of vials required based on patient's actual body weight for step-up dose 2 using TECVAYLI 30 mg/3 mL (10 mg/mL) vial.

Table 8: Step-up Dose 2 (0.3 mg/kg) Injection Volumes using TECVAYLI 30 mg/3 mL (10 mg/mL) Vial
Patient Body Weight (kg) | Total Dose (mg) | Volume of Injection (mL) | Number of Vials (1 vial=3 mL)
35 to 39 | 11 | 1.1 | 1
40 to 44 | 13 | 1.3 | 1
45 to 49 | 14 | 1.4 | 1
50 to 59 | 16 | 1.6 | 1
60 to 69 | 19 | 1.9 | 1
70 to 79 | 22 | 2.2 | 1
80 to 89 | 25 | 2.5 | 1
90 to 99 | 28 | 2.8 | 1
100 to 109 | 31 | 3.1 | 2
110 to 119 | 34 | 3.4 | 2
120 to 129 | 37 | 3.7 | 2
130 to 139 | 40 | 4 | 2
140 to 149 | 43 | 4.3 | 2
150 to 160 | 47 | 4.7 | 2

Use Table 9 to determine total dose, injection volume and number of vials required based on patient's actual body weight for the treatment dose using TECVAYLI 153 mg/1.7 mL (90 mg/mL) vial.

Table 9: Treatment Dose (1.5 mg/kg) Injection Volumes using TECVAYLI 153 mg/1.7 mL (90 mg/mL) Vial
Patient Body Weight (kg) | Total Dose (mg) | Volume of Injection (mL) | Number of Vials (1 vial=1.7 mL)
35 to 39 | 56 | 0.62 | 1
40 to 44 | 63 | 0.7 | 1
45 to 49 | 70 | 0.78 | 1
50 to 59 | 82 | 0.91 | 1
60 to 69 | 99 | 1.1 | 1
70 to 79 | 108 | 1.2 | 1
80 to 89 | 126 | 1.4 | 1
90 to 99 | 144 | 1.6 | 1
100 to 109 | 153 | 1.7 | 1
110 to 119 | 171 | 1.9 | 2
120 to 129 | 189 | 2.1 | 2
130 to 139 | 198 | 2.2 | 2
140 to 149 | 216 | 2.4 | 2
150 to 160 | 234 | 2.6 | 2

Remove the appropriate strength TECVAYLI vial from refrigerated storage [2 °C to 8 °C (36 °F to 46 °F)].

Once removed from refrigerated storage, equilibrate TECVAYLI to ambient temperature [15 °C to 30 °C (59 °F to 86 °F)] for at least 15 minutes. Do not warm TECVAYLI in any other way.

Once equilibrated, gently swirl the vial for approximately 10 seconds to mix. Do not shake.

Withdraw the required injection volume of TECVAYLI from the vial(s) into an appropriately sized syringe using a transfer needle.

Each injection volume should not exceed 2 mL. Divide doses requiring greater than 2 mL equally into multiple syringes.

TECVAYLI is compatible with stainless steel injection needles and polypropylene or polycarbonate syringe material.

Replace the transfer needle with an appropriately sized needle for injection.

Administration of TECVAYLI

Inject the required volume of TECVAYLI into the subcutaneous tissue of the abdomen (preferred injection site). Alternatively, TECVAYLI may be injected into the subcutaneous tissue at other sites (e.g., thigh). If multiple injections are required, TECVAYLI injections should be at least 2 cm apart.

Do not inject into tattoos or scars or areas where the skin is red, bruised, tender, hard or not intact.

Any unused product or waste material should be disposed in accordance with local requirements.

Storage

If the prepared dosing syringe(s) of TECVAYLI is not used immediately, store syringe(s) at 2 °C to 8 °C (36 °F to 46 °F) or at ambient temperature 15 °C to 30 °C (59 °F to 86 °F) for a maximum of 20 hours. Discard syringe(s) after 20 hours, if not used.

Monitoring

Due to the risk of CRS and neurologic toxicity, including ICANS, patients should be hospitalized for 48 hours after administration of all doses within the TECVAYLI step-up dosing schedule [see Dosage and Administration (2.1)and Warnings and Precautions (5.1, 5.2)] .

3 DOSAGE FORMS AND STRENGTHS

Injection

- 30 mg/3 mL (10 mg/mL) clear to slightly opalescent, colorless to light yellow solution in a single-dose vial.
- 153 mg/1.7 mL (90 mg/mL) clear to slightly opalescent, colorless to light yellow solution in a single-dose vial.

4 CONTRAINDICATIONS

None.

5 WARNINGS AND PRECAUTIONS

5.1 Cytokine Release Syndrome

TECVAYLI can cause cytokine release syndrome (CRS), including life-threatening or fatal reactions [see Adverse Reactions (6.1)] .

In the clinical trial, CRS occurred in 72% of patients who received TECVAYLI at the recommended dose, with Grade 1 CRS occurring in 50% of patients, Grade 2 in 21%, and Grade 3 in 0.6%. Recurrent CRS occurred in 33% of patients. Most patients experienced CRS following step-up dose 1 (42%), step-up dose 2 (35%), or the initial treatment dose (24%). Less than 3% of patients developed first occurrence of CRS following subsequent doses of TECVAYLI. The median time to onset of CRS was 2 (range: 1 to 6) days after the most recent dose with a median duration of 2 (range: 1 to 9) days.

Clinical signs and symptoms of CRS included, but were not limited to, fever, hypoxia, chills, hypotension, sinus tachycardia, headache, and elevated liver enzymes (aspartate aminotransferase and alanine aminotransferase elevation).

Initiate therapy according to TECVAYLI step-up dosing schedule to reduce risk of CRS [see Dosage and Administration (2.1, 2.4)] . Administer pretreatment medications to reduce risk of CRS and monitor patients following administration of TECVAYLI accordingly [see Dosage and Administration (2.2, 2.4)] .

At the first sign of CRS, immediately evaluate patient for hospitalization. Administer supportive care based on severity and consider further management per current practice guidelines. Withhold or permanently discontinue TECVAYLI based on severity [see Dosage and Administration (2.4)] .

TECVAYLI is available only through a restricted program under a REMS [see Warnings and Precautions (5.3)].

5.2 Neurologic Toxicity including ICANS

TECVAYLI can cause serious, life-threatening or fatal neurologic toxicity, including Immune Effector Cell-Associated Neurotoxicity Syndrome (ICANS) [see Adverse Reactions (6.1)] .

In the clinical trial, neurologic toxicity occurred in 57% of patients who received TECVAYLI at the recommended dose, with Grade 3 or 4 neurologic toxicity occurring in 2.4% of patients. The most frequent neurologic toxicities were headache (25%), motor dysfunction (16%), sensory neuropathy (15%), and encephalopathy (13%).

With longer follow-up, Grade 4 seizure and fatal Guillain-Barré syndrome (one patient each) occurred in patients who received TECVAYLI.

In the clinical trial, ICANS was reported in 6% of patients who received TECVAYLI at the recommended dose [see Adverse Reactions (6.1)] . Recurrent ICANS occurred in 1.8% of patients. Most patients experienced ICANS following step-up dose 1 (1.2%), step-up dose 2 (0.6%), or the initial treatment dose (1.8%). Less than 3% of patients developed first occurrence of ICANS following subsequent doses of TECVAYLI. The median time to onset of ICANS was 4 (range: 2 to 8) days after the most recent dose with a median duration of 3 (range: 1 to 20) days. The most frequent clinical manifestations of ICANS reported were confusional state and dysgraphia. The onset of ICANS can be concurrent with CRS, following resolution of CRS, or in the absence of CRS.

Monitor patients for signs and symptoms of neurologic toxicity during treatment. At the first sign of neurologic toxicity, including ICANS, immediately evaluate patient and provide supportive therapy based on severity. Withhold or permanently discontinue TECVAYLI based on severity per recommendations and consider further management per current practice guidelines [see Dosage and Administration (2.4)] .

Due to the potential for neurologic toxicity, patients receiving TECVAYLI are at risk of depressed level of consciousness [see Adverse Reactions (6.1)] . Advise patients to refrain from driving or operating heavy or potentially dangerous machinery during and for 48 hours after completion of TECVAYLI step-up dosing schedule and in the event of new onset of any neurologic toxicity symptoms until neurologic toxicity resolves [see Dosage and Administration (2.1)] .

TECVAYLI is available only through a restricted program under a REMS [see Warnings and Precautions (5.3)].

5.3 TECVAYLI and TALVEY REMS

TECVAYLI is available only through a restricted program under a REMS called the TECVAYLI and TALVEY REMS because of the risks of CRS and neurologic toxicity, including ICANS [see Warnings and Precautions (5.1, 5.2)].

Notable requirements of the TECVAYLI and TALVEY REMS include the following:

- Prescribers must be certified with the program by enrolling and completing training.
- Prescribers must counsel patients receiving TECVAYLI about the risk of CRS and neurologic toxicity, including ICANS, and provide patients with Patient Wallet Card.
- Pharmacies and healthcare settings that dispense TECVAYLI must be certified with the TECVAYLI and TALVEY REMS program and must verify prescribers are certified through the TECVAYLI and TALVEY REMS program.
- Wholesalers and distributers must only distribute TECVAYLI to certified pharmacies or healthcare settings.

Further information about the TECVAYLI and TALVEY REMS program is available at www.TEC-TALREMS.com or by telephone at 1-855-810-8064.

5.4 Hepatotoxicity

TECVAYLI can cause hepatotoxicity, including fatalities. In patients who received TECVAYLI at the recommended dose in the clinical trial, there was one fatal case of hepatic failure. Elevated aspartate aminotransferase (AST) occurred in 34% of patients, with Grade 3 or 4 elevations in 1.2%. Elevated alanine aminotransferase (ALT) occurred in 28% of patients, with Grade 3 or 4 elevations in 1.8%. Elevated total bilirubin occurred in 6% of patients with Grade 3 or 4 elevations in 0.6%. Liver enzyme elevation can occur with or without concurrent CRS.

Monitor liver enzymes and bilirubin at baseline and during treatment as clinically indicated. Withhold TECVAYLI or consider permanent discontinuation of TECVAYLI based on severity [see Dosage and Administration (2.4)].

5.5 Infections

TECVAYLI can cause severe, life-threatening, or fatal infections. In patients who received TECVAYLI at the recommended dose in the clinical trial, serious infections, including opportunistic infections, occurred in 30% of patients, with Grade 3 or 4 infections in 35%, and fatal infections in 4.2% [see Adverse Reactions (6.1)] .

Monitor patients for signs and symptoms of infection prior to and during treatment with TECVAYLI and treat appropriately. Administer prophylactic antimicrobials according to guidelines [see Dosage and Administration (2.2)] .

Withhold TECVAYLI or consider permanent discontinuation of TECVAYLI based on severity [see Dosage and Administration (2.4)] .

Monitor immunoglobulin levels during treatment with TECVAYLI and treat according to guidelines, including infection precautions and antibiotic or antiviral prophylaxis [see Dosage and Administration (2.2)] .

5.6 Neutropenia

TECVAYLI can cause neutropenia and febrile neutropenia. In patients who received TECVAYLI at the recommended dose in the clinical trial, decreased neutrophils occurred in 84% of patients, with Grade 3 or 4 decreased neutrophils in 56%. Febrile neutropenia occurred in 3% of patients [see Adverse Reactions (6.1)].

Monitor complete blood cell counts at baseline and periodically during treatment and provide supportive care per local institutional guidelines.

Monitor patients with neutropenia for signs of infection.

Withhold TECVAYLI based on severity [see Dosage and Administration (2.4)] .

5.7 Hypersensitivity and Other Administration Reactions

TECVAYLI can cause both systemic administration-related reactions and local injection-site reactions.

Systemic Reactions

In patients who received TECVAYLI at the recommended dose in the clinical trial, 1.2% of patients experienced systemic-administration reactions, which included Grade 1 recurrent pyrexia and Grade 1 swollen tongue.

Local Reactions

In patients who received TECVAYLI at the recommended dose in the clinical trial, injection-site reactions occurred in 35% of patients with Grade 1 injection-site reactions in 30% and Grade 2 in 4.8%.

Withhold TECVAYLI or consider permanent discontinuation of TECVAYLI based on severity [see Dosage and Administration (2.4)] .

5.8 Embryo-Fetal Toxicity

Based on its mechanism of action, TECVAYLI may cause fetal harm when administered to a pregnant woman. Advise pregnant women of the potential risk to the fetus. Advise females of reproductive potential to use effective contraception during treatment with TECVAYLI and for 5 months after the last dose [see Use in Specific Populations (8.1, 8.3)] .

6 ADVERSE REACTIONS

The following adverse reactions are also described elsewhere in the labeling:

- Cytokine Release Syndrome [see Warnings and Precautions (5.1)]
- Neurologic Toxicity including ICANS [see Warnings and Precautions (5.2)]
- Hepatotoxicity [see Warnings and Precautions (5.4)]
- Infections [see Warnings and Precautions (5.5)]
- Neutropenia [see Warnings and Precautions (5.6)]
- Hypersensitivity and Other Administration Reactions [see Warnings and Precautions (5.7)]

6.1 Clinical Trials Experience

Because clinical trials are conducted under widely varying conditions, adverse reaction rates observed in the clinical trials of a drug cannot be directly compared to rates in the clinical trials of another drug and may not reflect the rates observed in practice.

Relapsed/Refractory Multiple Myeloma

MajesTEC-1

The safety of TECVAYLI was evaluated in MajesTEC-1 [see Clinical Studies (14)] which included adult patients with relapsed or refractory multiple myeloma. Patients received step-up doses of 0.06 mg/kg and 0.3 mg/kg of TECVAYLI followed by TECVAYLI 1.5 mg/kg, subcutaneously once weekly (N=165). Among patients who received TECVAYLI, 47% were exposed for 6 months or longer and 7% were exposed for one year or longer.

The median age of patients who received TECVAYLI was 64 years (range: 33 to 84 years); 58% were male; 81% were White, 13% were Black or African American, and 2% were Asian.

Serious adverse reactions occurred in 54% of patients who received TECVAYLI. Serious adverse reactions in >2% of patients included pneumonia (15%), cytokine release syndrome (8%), sepsis (6%), general physical health deterioration (6%), COVID-19 (6%), acute kidney injury (4.8%), pyrexia (4.8%), musculoskeletal pain (2.4%), and encephalopathy (2.4%).

Fatal adverse reactions occurred in 5% of patients who received TECVAYLI, including COVID-19 (1.8%), pneumonia (1.8%), septic shock (0.6%), acute renal failure (0.6%), and hemoperitoneum (0.6%).

Permanent discontinuation of TECVAYLI due to adverse reactions occurred in 1.2% of patients. Adverse reactions resulting in permanent discontinuation of TECVAYLI included pneumonia (adenoviral and pneumocystis jirovecii pneumonia in the same patient) and hypercalcemia.

Dosage interruptions of TECVAYLI due to an adverse reaction occurred in 73% of patients. Adverse reactions which required dosage interruption in >5% of patients included neutropenia, pneumonia, pyrexia, cytokine release syndrome, upper respiratory tract infection, and COVID-19.

The most common adverse reactions (≥20%) were pyrexia, CRS, musculoskeletal pain, injection site reaction, fatigue, upper respiratory tract infection, nausea, headache, pneumonia, and diarrhea. The most common Grade 3 to 4 laboratory abnormalities (≥20%) were decreased lymphocytes, decreased neutrophils, decreased white blood cells, decreased hemoglobin, and decreased platelets.

Table 10 summarizes the adverse reactions in MajesTEC-1.

Table 10: Adverse Reactions (≥10%) in Patients with Multiple Myeloma Who Received TECVAYLI in MajesTEC-1
Adverse Reactions | TECVAYLI (N=165)
Adverse Reactions | Any Grade (%) | Grade 3 or 4 (%)
General disorders and administration site conditions
Pyrexia | 76 | 3 [Only grade 3 adverse reactions occurred.]
Injection site reaction [Injection site reaction includes application site erythema, injection site bruising, injection site cellulitis, injection site discomfort, injection site erythema, injection site hematoma, injection site induration, injection site inflammation, injection site edema, injection site pruritus, injection site rash, injection site reaction and injection site swelling.] | 37 | 0.6
Fatigue [Fatigue includes asthenia and fatigue.] | 33 | 2.4
Chills | 16 | 0
Pain [Pain includes ear pain, flank pain, groin pain, oropharyngeal pain, pain, pain in jaw, toothache and tumor pain.] | 15 | 1.8
Edema [Edema includes face edema, fluid overload, fluid retention, edema peripheral and peripheral swelling.] | 13 | 0
Immune system disorders
Cytokine release syndrome | 72 | 0.6
Hypogammaglobulinemia [Hypogammaglobulinemia includes hypogammaglobulinemia and hypoglobulinemia.] | 11 | 1.2
Musculoskeletal and connective tissue disorders
Musculoskeletal pain [Musculoskeletal pain includes arthralgia, back pain, muscle discomfort, musculoskeletal chest pain, musculoskeletal pain, myalgia, neck pain, non-cardiac chest pain and pain in extremity.] | 44 | 4.2
Bone pain | 16 | 3
Infections
Upper respiratory tract infection [Upper respiratory tract infection includes bronchitis, influenza like illness, nasopharyngitis, pharyngitis, respiratory tract infection, respiratory tract infection bacterial, rhinitis, rhinovirus infection, sinusitis, tracheitis, upper respiratory tract infection and viral upper respiratory tract infection.] | 26 | 2.4
Pneumonia [Pneumonia includes COVID-19 pneumonia, enterobacter pneumonia, lower respiratory tract infection, metapneumovirus pneumonia, pneumocystis jirovecii pneumonia, pneumonia, pneumonia adenoviral, pneumonia klebsiella, pneumonia moraxella, pneumonia pneumococcal, pneumonia pseudomonal, pneumonia respiratory syncytial viral, pneumonia staphylococcal and pneumonia viral.] [Includes the following fatal adverse reactions: hemorrhage (n=1), pneumonia (n=3).] | 24 | 15
Urinary tract infection [Urinary tract infection includes cystitis, cystitis escherichia, cystitis klebsiella, escherichia urinary tract infection, urinary tract infection and urinary tract infection bacterial.] | 11 | 5
Gastrointestinal disorders
Nausea | 25 | 0.6
Diarrhea | 21 | 2.4
Constipation | 18 | 0
Vomiting | 12 | 0.6
Nervous system disorders
Headache | 25 | 0.6
Motor dysfunction [Motor dysfunction includes cogwheel rigidity, dysgraphia, dysphonia, gait disturbance, hypokinesia, muscle rigidity, muscle spasms, muscular weakness, peroneal nerve palsy, psychomotor hyperactivity, tremor and VI th nerve paralysis.] | 16 | 0
Sensory neuropathy [Sensory neuropathy includes dysesthesia, hypoesthesia, hypoesthesia oral, neuralgia, paresthesia, paresthesia oral, peripheral sensory neuropathy, sciatica and vestibular neuronitis.] | 15 | 1.2
Encephalopathy [Encephalopathy includes agitation, apathy, aphasia, confusional state, delirium, depressed level of consciousness, disorientation, dyscalculia, hallucination, lethargy, memory impairment, mental status changes and somnolence.] | 13 | 0
Vascular disorders
Hypotension | 18 | 1.2
Hemorrhage [Hemorrhage includes conjunctival hemorrhage, epistaxis, hematoma, hematuria, hemoperitoneum, hemorrhoidal hemorrhage, lower gastrointestinal hemorrhage, melena, mouth hemorrhage and subdural hematoma.] | 12 | 1.8
Hypertension [Hypertension includes essential hypertension and hypertension.] | 12 | 4.8
Respiratory, thoracic, and mediastinal disorders
Hypoxia | 18 | 1.8
Cough [Cough includes allergic cough, cough, productive cough and upper-airway cough syndrome.] | 15 | 0
Cardiac disorders
Cardiac arrhythmia [Cardiac arrhythmia includes atrial flutter, cardiac arrest, sinus bradycardia, sinus tachycardia, supraventricular tachycardia, tachycardia and ventricular tachycardia.] | 16 | 1.8
Metabolism and nutrition disorders
Decreased appetite | 11 | 0.6
Renal and urinary disorders
Acute kidney injury [Acute kidney injury includes acute kidney injury and renal impairment.] | 11 | 3.6
Adverse reactions were graded based on CTCAE Version 4.03, with the exception of CRS, which was graded per ASTCT 2019 criteria.

Clinically relevant adverse reactions in <10% of patients who received TECVAYLI included febrile neutropenia, sepsis, ICANS, seizure, Guillain-Barré syndrome, hepatic failure, and new onset or reactivated viral infections (including adenovirus, hepatitis B virus (HBV), cytomegalovirus (CMV), varicella zoster virus (VZV), herpes simplex virus (HSV), and progressive multifocal leukoencephalopathy (PML).

Table 11 summarizes laboratory abnormalities in MajesTEC-1.

Table 11: Select Laboratory Abnormalities (≥30%) That Worsened from Baseline in Patients with Multiple Myeloma Who Received TECVAYLI in MajesTEC-1
Laboratory Abnormality | TECVAYLI (N=165 [The denominator used to calculate the rate varied from 164 to 165 based on the number of patients with a baseline value and at least one post-treatment value.])
Laboratory Abnormality | All Grades (%) | Grade 3 or 4 (%)
Hematology
Lymphocyte count decreased | 92 | 84
White blood cell decreased | 86 | 41
Neutrophil count decreased | 84 | 56
Platelet count decreased | 71 | 22
Hemoglobin decreased | 67 | 33
Chemistry
Albumin decreased | 68 | 6
Alkaline phosphatase increased | 42 | 2.4
Phosphorus decreased | 38 | 13
Gamma-glutamyl transferase increased | 37 | 8
Sodium decreased | 35 | 10
Aspartate aminotransferase increased | 34 | 1.2
Calcium (corrected) decreased | 31 | 1.2
Creatinine increased | 30 | 3
Laboratory toxicity grades are derived based on the NCI CTCAE (National Cancer Institute Common Terminology Criteria for Adverse Events) Version 4.03.

7 DRUG INTERACTIONS

TECVAYLI causes release of cytokines [see Clinical Pharmacology (12.2)] that may suppress activity of cytochrome P450 (CYP) enzymes, resulting in increased exposure of CYP substrates. The highest risk of drug-drug interaction is expected to occur from initiation of TECVAYLI step-up dosing schedule up to 7 days after the first treatment dose and during and after CRS [see Warnings and Precautions (5.1)] . Monitor for toxicity or concentrations of drugs that are CYP substrates where minimal concentration changes may lead to serious adverse reactions. Adjust the dose of the concomitant CYP substrate drug as needed.

8 USE IN SPECIFIC POPULATIONS

8.1 Pregnancy

Risk Summary

Based on the mechanism of action, TECVAYLI may cause fetal harm when administered to a pregnant woman [see Clinical Pharmacology (12.1)] . There are no available data on the use of TECVAYLI in pregnant women to evaluate for a drug associated risk. No animal reproductive or developmental toxicity studies have been conducted with TECVAYLI. Teclistamab-cqyv causes T-cell activation and cytokine release; immune activation may compromise pregnancy maintenance. Human immunoglobulin G (IgG) is known to cross the placenta; therefore, teclistamab-cqyv has the potential to be transmitted from the mother to the developing fetus. Advise women of the potential risk to the fetus.

TECVAYLI is associated with hypogammaglobulinemia, therefore, assessment of immunoglobulin levels in newborns of mothers treated with TECVAYLI should be considered.

In the U.S. general population, the estimated background risk of major birth defects and miscarriage in clinically recognized pregnancies is 2% to 4% and 15% to 20%, respectively.

8.2 Lactation

Risk Summary

There are no data on the presence of teclistamab-cqyv in human milk, the effect on the breastfed child, or the effects on milk production. Maternal IgG is known to be present in human milk. The effects of local gastrointestinal exposure and limited systemic exposure in the breastfed child to TECVAYLI are unknown. Because of the potential for serious adverse reactions in a breastfed child, advise women not to breastfeed during treatment with TECVAYLI and for 5 months after the last dose.

8.3 Females and Males of Reproductive Potential

TECVAYLI may cause fetal harm when administered to a pregnant woman [see Use in Specific Populations (8.1)] .

Pregnancy Testing

Verify pregnancy status of females of reproductive potential prior to initiating TECVAYLI.

Contraception

Females

Advise females of reproductive potential to use effective contraception during treatment and for 5 months after the last dose of TECVAYLI.

8.4 Pediatric Use

The safety and efficacy of TECVAYLI have not been established in pediatric patients.

8.5 Geriatric Use

Of the 165 patients with relapsed or refractory multiple myeloma treated with TECVAYLI in MajesTEC-1 at the recommended dosage, 48% were 65 years of age or older, and 15% were 75 years of age or older. No overall differences in safety or effectiveness were observed between patients 65 to 74 years of age compared to younger patients. There is an insufficient number of patients 75 years of age or older to assess whether there are differences in safety or effectiveness.

11 DESCRIPTION

Teclistamab-cqyv, a bispecific B-cell maturation antigen (BCMA)-directed CD3 T-cell engager, is a humanized immunoglobulin G4-proline, alanine, alanine (IgG4-PAA) antibody. Teclistamab-cqyv is produced in Chinese Hamster Ovary (CHO) cells using recombinant DNA technology. Teclistamab-cqyv consists of an anti-BCMA heavy chain and light chain and an anti-CD3 heavy chain and light chain with two interchain disulfide bonds connecting the two arms. The molecular weight of teclistamab-cqyv is approximately 146 kDa.

TECVAYLI®(teclistamab-cqyv) injection is a sterile, preservative-free, clear to slightly opalescent, colorless to light yellow solution supplied in a single-dose vial for subcutaneous administration.

Each TECVAYLI 3 mL single-dose vial contains 30 mg of teclistamab-cqyv, edetate disodium (0.054 mg), glacial acetic acid (0.72 mg), polysorbate 20 (1.2 mg), sodium acetate (2.7 mg), sucrose (240 mg), and Water for Injection, USP.

Each TECVAYLI 1.7 mL single-dose vial contains 153 mg of teclistamab-cqyv, edetate disodium (0.031 mg), glacial acetic acid (0.41 mg), polysorbate 20 (0.68 mg), sodium acetate (1.5 mg), sucrose (140 mg), and Water for Injection, USP.

12 CLINICAL PHARMACOLOGY

12.1 Mechanism of Action

Teclistamab-cqyv is a bispecific T-cell engaging antibody that binds to the CD3 receptor expressed on the surface of T-cells and B-cell maturation antigen (BCMA) expressed on the surface of multiple myeloma cells and some healthy B-lineage cells.

In vitro, teclistamab-cqyv activated T-cells, caused the release of various proinflammatory cytokines, and resulted in the lysis of multiple myeloma cells.

12.2 Pharmacodynamics

Serum concentrations of cytokines (IL-6, IL-10, TNF-α, and IFN-γ) and IL-2R were measured before and after administration of step-up dose 1, step-up dose 2, and the first three treatment doses of TECVAYLI. Increased concentrations of IL-6, IL-10, and IL-2R were observed during this period.

12.3 Pharmacokinetics

The Cmaxand AUCtauof teclistamab-cqyv after the first subcutaneous treatment dose increase proportionally over a dosage range of 0.08 mg/kg to 3 mg/kg (0.05 to 2 times the approved recommended treatment dosage). Ninety percent of steady state exposure was achieved after 12 weekly treatment doses. The mean accumulation ratio between the first and 13thweekly treatment dose of teclistamab-cqyv 1.5 mg/kg was 4.2-fold for Cmax, 4.1-fold for Ctrough, and 5.3-fold for AUCtau.

The Cmax, Ctrough, and AUCtauof teclistamab-cqyv are presented in Table 12.

Table 12: Pharmacokinetic Parameters of Teclistamab-cqyv for the 13thWeekly Treatment Dose of 1.5 mg/kg [Following administration of teclistamab-cqyv in patients with relapsed or refractory multiple myeloma (MajesTEC-1).]
Pharmacokinetic Parameter | Teclistamab-cqyv Geometric Mean (CV%)
Cmax(mcg/mL) | 23.8 (55%)
Ctrough(mcg/mL) | 21.1 (63%)
AUCtau(mcg∙h/mL) | 3,838 (57%)
SD = standard deviation; Cmax= Maximum serum teclistamab-cqyv concentration; Ctrough= Serum teclistamab-cqyv concentration prior to next dose; CV = geometric coefficient of variation; AUCtau= Area under the concentration-time curve over the weekly dosing interval.

Absorption

The mean bioavailability of teclistamab-cqyv was 72% when administered subcutaneously. The median (range) Tmaxof teclistamab-cqyv after the first and 13thweekly treatment doses were 139 (19 to 168) hours and 72 (24 to 168) hours, respectively.

Distribution

The mean (coefficient of variation [CV]%) volume of distribution of teclistamab-cqyv was 5.63 L (29%).

Elimination

Teclistamab-cqyv clearance decreases over time, with a mean (CV%) maximal reduction from baseline to the 13thweekly treatment dose of 40.8% (56%). The geometric mean (CV%) clearance is 0.472 L/day (64%) at the 13thweekly treatment dose. Patients who discontinue teclistamab-cqyv after the 13thweekly treatment dose are expected to have a 50% reduction from Cmaxin teclistamab-cqyv concentration at a median (5thto 95thpercentile) time of 15 (7 to 33) days after Tmaxand a 97% reduction from Cmaxin teclistamab-cqyv concentration at a median time of 69 (32 to 163) days after Tmax.

Specific Populations

The volume of distribution and clearance of teclistamab-cqyv increase with increasing body weight (41 kg to 139 kg).

There were no clinically significant differences in the pharmacokinetics of teclistamab-cqyv based on age (24 to 84 years), sex, race (White, Black or African American), ethnicity (Hispanic/Latino, not Hispanic/Latino), mild or moderate renal impairment (estimated glomerular filtration rate [eGFR] by Modification of Diet in Renal Disease [MDRD] method: 30 to 89 mL/min), or mild hepatic impairment (total bilirubin less than or equal to upper limit of normal [ULN] with AST greater than ULN or total bilirubin greater than 1 to 1.5 times ULN with any AST). The effects of severe renal impairment (eGFR less than 30 mL/min) or moderate to severe hepatic impairment (total bilirubin greater than 1.5 times ULN with any AST) on the pharmacokinetics of teclistamab-cqyv are unknown.

Drug Interaction Studies

No clinical studies evaluating the drug interaction potential of teclistamab-cqyv have been conducted.

12.6 Immunogenicity

The observed incidence of anti-drug antibodies is highly dependent on the sensitivity and specificity of the assay. Differences in assay methods preclude meaningful comparisons of the incidence of anti-drug antibodies in the studies described below with the incidence of anti-drug antibodies in other studies, including those of teclistamab-cqyv or of other teclistamab products.

During treatment in MajesTEC-1 (up to 27 months), 1/186 (0.5%) of patients treated with subcutaneous TECVAYLI at various dosages developed anti-teclistamab-cqyv antibodies. Because of the low occurrence of anti-drug antibodies, the effect of these antibodies on the pharmacokinetics, pharmacodynamics, safety, and/or effectiveness of teclistamab products is unknown.

13 NONCLINICAL TOXICOLOGY

13.1 Carcinogenesis, Mutagenesis, Impairment of Fertility

No carcinogenicity or genotoxicity studies have been conducted with teclistamab-cqyv.

No studies have been conducted to evaluate the effects of teclistamab-cqyv on fertility.

14 CLINICAL STUDIES

The efficacy of TECVAYLI was evaluated in patients with relapsed or refractory multiple myeloma in a single-arm, open-label, multi-center study (MajesTEC-1, NCT03145181 [Phase 1] and NCT04557098 [Phase 2]). The study included patients who had previously received at least three prior therapies, including a proteasome inhibitor, an immunomodulatory agent, and an anti-CD38 monoclonal antibody. The study excluded patients who had stroke, seizure, allogeneic stem cell transplantation within the past 6 months, Eastern Cooperative Oncology Group (ECOG) performance score of 2 or higher, known active CNS involvement or clinical signs of meningeal involvement of multiple myeloma, or active or documented history of autoimmune disease, with the exception of vitiligo, Type 1 diabetes, and prior autoimmune thyroiditis.

Patients received step-up doses of 0.06 mg/kg and 0.3 mg/kg of TECVAYLI followed by TECVAYLI 1.5 mg/kg subcutaneously once weekly thereafter until disease progression or unacceptable toxicity [see Dosage and Administration (2.1)] .

The efficacy population included 110 patients. The median age was 66 (range: 33 to 82) years with 16% of patients 75 years of age or older; 56% were male; 91% were White, 5% were Black or African American, 3% were Asian. The International Staging System (ISS) at study entry was Stage I in 50%, Stage II in 38%, and Stage III in 12% of patients. High-risk cytogenetics (presence of del(17p), t(4;14) and t(14;16)) were present in 25% of patients. Seventeen percent of patients had extramedullary plasmacytomas. Patients with prior BCMA-targeted therapy were not included in the efficacy population.

The median number of prior lines of therapy was 5 (range: 2 to 14); 78% of patients had received at least 4 prior lines of therapy. Eighty-one percent of patients received prior stem cell transplantation. All patients had received prior therapy with a proteasome inhibitor, an immunomodulatory agent and an anti-CD38 monoclonal antibody, and 76% were triple-class refractory (refractory to a proteasome inhibitor, an immunomodulatory agent and an anti-CD38 monoclonal antibody).

Efficacy was established based on overall response rate (ORR) as determined by the Independent Review Committee (IRC) assessment using International Myeloma Working Group (IMWG) 2016 criteria (see Table 13).

The median time to first response was 1.2 months (range: 0.2 to 5.5 months). With a median follow-up of 7.4 months among responders, the estimated duration of response (DOR) rate was 90.6% (95% CI: 80.3%, 95.7%) at 6 months and 66.5% (95% CI: 38.8%, 83.9%) at 9 months.

Table 13: Efficacy Results for MajesTEC-1
 | N=110
Overall response rate (ORR: sCR+CR+VGPR+PR) n(%) | 68 (61.8)
95% CI (%) | (52.1, 70.9)
Complete response (CR) or better [Complete response or better = Stringent complete response (sCR) + complete response (CR).] | 31 (28.2)
Very good partial response (VGPR) | 32 (29.1)
Partial response (PR) | 5 (4.5)
Duration of Response (DOR) (months)
DOR (Months): Median (95% CI) | NE (9.0, NE)
NE=not estimable

16 HOW SUPPLIED/STORAGE AND HANDLING

TECVAYLI®(teclistamab-cqyv) injection is a sterile, preservative-free, clear to slightly opalescent, colorless to light yellow solution supplied as follows:

- One 30 mg/3 mL (10 mg/mL) single-dose vial in a carton: NDC: 57894-449-01
- One 153 mg/1.7 mL (90 mg/mL) single-dose vial in a carton: NDC: 57894-450-01

STORAGE AND HANDLING

Store refrigerated at 2 °C to 8 °C (36 °F to 46 °F) in the original carton to protect from light.

Do not freeze.

17 PATIENT COUNSELING INFORMATION

Advise the patient to read the FDA-approved patient labeling (Medication Guide).

Cytokine Release Syndrome (CRS)

Discuss the signs and symptoms associated with CRS, including fever, hypoxia, chills, hypotension, sinus tachycardia, headache, and elevated liver enzymes. Advise patients to immediately contact their healthcare provider if they experience any signs or symptoms of CRS. Advise patients that they will be hospitalized for 48 hours after administration of all doses within the TECVAYLI step-up dosing schedule [see Dosage and Administration (2.4)and Warnings and Precautions (5.1)].

Neurologic Toxicity including ICANS

Discuss the signs and symptoms associated with neurologic toxicity, including ICANS, including headache, confusion, dysgraphia, motor dysfunction, neuropathy, or encephalopathy. Advise patients to immediately contact their healthcare provider if they experience any signs or symptoms of neurologic toxicity. Advise patients to refrain from driving or operating heavy or potentially dangerous machinery during and for 48 hours after completion of TECVAYLI step-up dosing schedule and in the event of new onset of any neurologic toxicity symptoms until neurologic toxicity resolves [see Dosage and Administration (2.4)and Warnings and Precautions (5.2)].

TECVAYLI and TALVEY REMS

TECVAYLI is available only through a restricted program called TECVAYLI and TALVEY REMS. Inform patients that they will be given a Patient Wallet Card that they should carry with them at all times and show to all of their healthcare providers. This card describes signs and symptoms of CRS and neurologic toxicity which, if experienced, should prompt the patient to immediately seek medical attention [see Warnings and Precautions (5.3)].

Hepatotoxicity

Advise patients that liver enzyme elevations may occur and that they should report symptoms that may indicate liver toxicity, including fatigue, anorexia, right upper abdominal discomfort, dark urine, or jaundice [see Warnings and Precautions (5.4)].

Infections

Discuss the signs and symptoms of infection [see Dosage and Administration (2.4)and Warnings and Precautions (5.5)] .

Neutropenia

Discuss the signs and symptoms associated with neutropenia and febrile neutropenia [see Dosage and Administration (2.4)and Warnings and Precautions (5.6)] .

Hypersensitivity and Other Administration Reactions

Advise patients to immediately seek medical attention for any signs and symptoms of systemic administration-related reactions. Advise patients that local injection-site reactions may occur and to report any severe reactions [see Warnings and Precautions (5.7)].

Embryo-Fetal Toxicity

Advise pregnant women and females of reproductive potential of the potential risk to a fetus. Advise females of reproductive potential to inform their healthcare provider if they are pregnant or become pregnant. Advise females of reproductive potential to use effective contraception during treatment with TECVAYLI and for 5 months after the last dose [see Warnings and Precautions (5.8)and Use in Specific Populations (8.1, 8.3)] .

Lactation

Advise women not to breastfeed during treatment with TECVAYLI and for 5 months after the last dose [see Use in Specific Populations (8.2)] .

Manufactured by:
Janssen Biotech, Inc.
Horsham, PA 19044, USA
U.S. License Number 1864

For patent information: www.janssenpatents.com

© Johnson & Johnson and its affiliates 2022

MEDICATION GUIDE
TECVAYLI®[tek vay' lee]
(teclistamab-cqyv) injection, for subcutaneous use

What is the most important information I should know about TECVAYLI?

TECVAYLI may cause side effects that are serious, life-threatening or lead to death, including Cytokine Release Syndrome (CRS) and Neurologic problems.
Call your healthcare provider right away if you develop any of the signs or symptoms of CRS or neurologic problems listed below at any time during your treatment with TECVAYLI:
Cytokine Release Syndrome (CRS). Signs and symptoms of CRS may include:

- fever (100.4 °F or higher)
- difficulty breathing
- chills
- dizziness or lightheadedness
- fast heartbeat

- feeling anxious
- confusion or restlessness
- headache
- increased liver enzymes in your blood

Neurologic problems. Symptoms of neurologic problems with TECVAYLI include:

- headache
- jerking movements
- rigid muscles
- feeling restless
- numbness and tingling (feeling like "pins and needles")

- confusion
- trouble speaking
- muscle spasms
- tremor
- double vision

- changes in your handwriting
- problems walking
- muscle weakness in your body or face
- hearing loss
- burning, throbbing, or stabbing pain

- Due to the risk of CRS and neurologic symptoms, you should be hospitalized for 48 hours after all doses of TECVAYLI that are part of the "step-up dosing schedule." The "step-up dosing schedule" is when you receive the first 2 doses of TECVAYLI, which are called "step-up" doses, and then you receive the first "treatment dose" of TECVAYLI. After "step-up" dose 1 of TECVAYLI, the dose of TECVAYLI is increased. After "step-up" dose 2, the dose is increased again when you receive the first "treatment dose" of TECVAYLI.
  - "Step-up dose 1" is given on day 1 of treatment. "Step-up dose 2" is usually given on day 4 of treatment. The first "treatment dose" is usually given on day 7 of treatment.
  - Your healthcare provider will decide when you will receive "step-up dose 2" and your first "treatment dose."
    - "Step-up" dose 2 may be given between 2 to 4 days after "step-up" dose 1, or up to 7 days after "step-up" dose 1 if you have certain side effects with TECVAYLI.
    - Your first "treatment dose" may be given between 2 to 4 days after "step-up" dose 2, or up to 7 days after "step-up" dose 2 if you have certain side effects with TECVAYLI.
  - Your healthcare provider will decide the number of days to wait between your doses of TECVAYLI as well as how many treatments you will receive.
  - If your dose of TECVAYLI is delayed for any reason, you may need to repeat the "step-up dosing schedule" to receive TECVAYLI.
  - Before each "step-up" dose and your first "treatment dose" of TECVAYLI you will receive medicines to help reduce your risk of CRS. Your healthcare provider will decide if you need to receive medicines to help reduce your risk of CRS with future doses.
- Your healthcare provider will monitor you for signs and symptoms of CRS and neurologic problems during treatment with TECVAYLI, as well as other side effects and treat you as needed.
- Do not drive or operate heavy or dangerous machinery during and for 48 hours after your TECVAYLI "step-up dosing schedule" is completed, or at any time during treatment with TECVAYLI if you develop new neurologic symptoms until the symptoms go away.

TECVAYLI is available only through the TECVAYLI and TALVEY Risk Evaluation and Mitigation Strategy (REMS) due to the risk of CRS and neurologic problems.
You will receive a Patient Wallet Card from your healthcare provider. Carry the Patient Wallet Card with you at all times and show it to all of your healthcare providers.The Patient Wallet Card lists signs and symptoms of CRS and neurologic problems.
Get medical help right away if you develop any of the signs and symptoms listed on the Patient Wallet Card.You may need to be treated in a hospital.

- If you have any questions about TECVAYLI, ask your healthcare provider.
- Your healthcare provider may temporarily stop or completely stop your treatment with TECVAYLI if you develop CRS, neurologic problems or any other side effects that are severe.

See " What are the possible side effects of TECVAYLI?" for more information about side effects.

What is TECVAYLI?
TECVAYLI is a prescription medicine to treat adults with multiple myeloma who:

- have already received at least 4 treatment regimens, including a proteasome inhibitor, an immunomodulatory agent and an anti-CD38 monoclonal antibody to treat their multiple myeloma, and
- their cancer has come back or did not respond to prior treatment

It is not known if TECVAYLI is safe and effective in children.

Before you receive TECVAYLI, tell your healthcare provider about all of your medical conditions, including if you:

- have an infection
- are pregnant or plan to become pregnant. TECVAYLI may harm your unborn baby.
  - Your healthcare provider should do a pregnancy test before you start treatment with TECVAYLI.
  - You should use effective birth control (contraception) during treatment and for 5 months after your last dose of TECVAYLI.
  - Tell your healthcare provider right away if you become pregnant or think that you may be pregnant during treatment with TECVAYLI.
- are breastfeeding or plan to breastfeed. It is not known if TECVAYLI passes into your breast milk. Do not breastfeed during treatment and for 5 months after your last dose of TECVAYLI.

Tell your healthcare provider about all the medicines you take,including prescription and over-the-counter medicines, vitamins, and herbal supplements.

How will I receive TECVAYLI?

- TECVAYLI will be given to you by your healthcare provider as an injection under your skin (subcutaneous injection), usually in your stomach-area (abdomen), your thigh or another area of your body may be injected.
- See " What is the most important information I should know" at the beginning of this Medication Guide for information about how you will receive TECVAYLI.
- If you miss any appointments, call your healthcare provider as soon as possible to reschedule your appointment. It is important for you to be monitored closely for side effects during treatment with TECVAYLI.

What are the possible side effects of TECVAYLI?
TECVAYLI may cause serious side effects, including:

- See " What is the most important information I should know about TECVAYLI?"
- Liver problems. TECVAYLI can cause liver problems that may lead to death. Increased bilirubin and liver enzymes in your blood are common with TECVAYLI and can also sometimes be severe These increases in liver enzymes can happen with or without you also having CRS. Your healthcare provider will monitor you for these problems before you start and during treatment with TECVAYLI. Tell your healthcare provider if you develop any symptoms of a liver problem including:

- tiredness
- loss of appetite

- pain in your right upper stomach-area (abdomen)
- dark urine
- yellowing of your skin or white part of your eyes

- Infections.Upper respiratory tract infections and pneumonia are common with TECVAYLI. TECVAYLI can cause bacterial and viral infections that are severe, life-threatening, or that may lead to death.
  - Your healthcare provider will monitor you for signs and symptoms of infection before and during treatment with TECVAYLI.
  - Your healthcare provider may prescribe medicines for you to help prevent infections and treat you as needed if you develop an infection during treatment with TECVAYLI.
  - Tell your healthcare provider right away if you get a fever, chills or any signs or symptoms of an infection.
- Decreased white blood cell counts.Decreased white blood cell counts are common with TECVAYLI and can also be severe. Fever sometimes also happens with low white blood cell counts and may be a sign that you have an infection. Your healthcare provider will check your blood cell counts before you start and during treatment with TECVAYLI, and treat you as needed.
- Allergic reactions and injection site reactions.TECVAYLI can cause allergic reactions that can affect your whole body (systemic), and also cause injection site reactions.
  - Some people taking TECVAYLI can develop symptoms of an allergic reaction that can affect your whole body and may include fever or a swollen tongue. Get medical help right away if you develop symptoms of an allergic reaction during treatment with TECVAYLI.
  - Injection site reactions are common with TECVAYLI and can include: redness, heat, swelling, bruising, bacterial skin infection (cellulitis), discomfort, blood collection under the skin at the injection site (hematoma), and rash. Tell your healthcare provider if you develop any severe injection site reactions.

Your healthcare provider may temporarily or permanently stop TECVAYLI if you have any of the side effects listed above and they are severe.
The most common side effects of TECVAYLI include:

- fever
- pain in your joints and muscles, back and chest muscles, and in your arms and legs
- tiredness and weakness

- upper respiratory tract infections and pneumonia. See " Infections" above.
- nausea
- headache
- diarrhea

The most common severe abnormal lab test results with TECVAYLI include: decreased white blood cells, red blood cells and platelets.
These are not all the possible side effects of TECVAYLI.
Call your doctor for medical advice about side effects. You may report side effects to FDA at 1-800-FDA-1088.

General Information about TECVAYLI.
Medicines are sometimes prescribed for purposes other than those listed in a Medication Guide.
You can ask your healthcare provider for information about TECVAYLI that is written for health professionals.

What are the ingredients of TECVAYLI?
Active ingredient: teclistamab-cqyv
Inactive ingredients: edetate disodium, glacial acetic acid, polysorbate 20, sodium acetate, sucrose, Water for Injection
Manufactured by: Janssen Biotech, Inc., Horsham, PA 19044, USA
U.S. License Number 1864
For patent information: www.janssenpatents.com
© Johnson & Johnson and its affiliates 2022
For more information about TECVAYLI go to www.TECVAYLI.com or call 1-800-526-7736.

This Medication Guide has been approved by the U.S. Food and Drug Administration.

Revised: Aug 2025

PRINCIPAL DISPLAY PANEL - 30 mg/3 mL Vial Carton

Rx only
One Vial

NDC 57894-449-01

TECVAYLI®
(teclistamab-cqyv)
Injection

30 mg/3 mL
(10 mg/mL)

TECVAYLI®vials of different
concentrations should not be
combined to achieve treatment dose.

For subcutaneous injection
by a healthcare provider only.

Attention: Dispense the enclosed
Medication Guide to each patient.

Single-dose vial
Discard unused portion.

janssen

PRINCIPAL DISPLAY PANEL - 153 mg/1.7 mL Vial Carton

Rx only
One Vial

NDC 57894-450-01

TECVAYLI®
(teclistamab-cqyv)
Injection

153 mg/1.7 mL
(90 mg/mL)

TECVAYLI®vials of different
concentrations should not be
combined to achieve treatment dose.

For subcutaneous injection
by a healthcare provider only.

Attention: Dispense the enclosed
Medication Guide to each patient.

Single-dose vial
Discard unused portion.

janssen